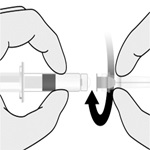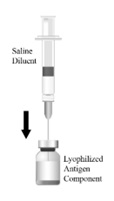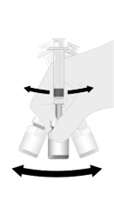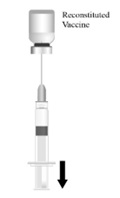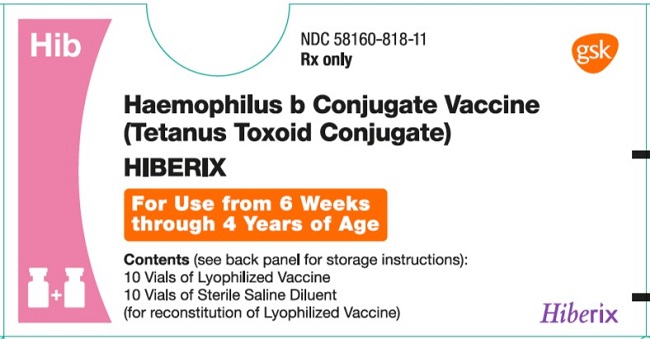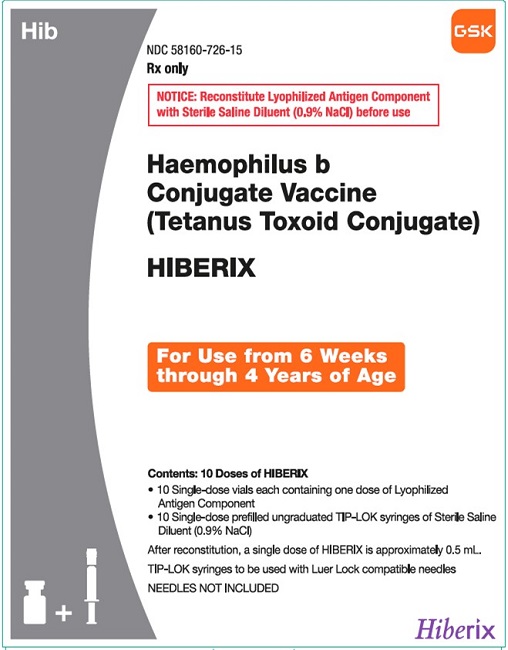 DRUG LABEL: Hiberix
NDC: 58160-818 | Form: KIT | Route: INTRAMUSCULAR
Manufacturer: GlaxoSmithKline Biologicals SA
Category: other | Type: VACCINE LABEL
Date: 20250121

ACTIVE INGREDIENTS: HAEMOPHILUS INFLUENZAE TYPE B STRAIN 20752 CAPSULAR POLYSACCHARIDE TETANUS TOXOID CONJUGATE ANTIGEN 10 ug/0.5 mL; WATER 1 mL/1 mL
INACTIVE INGREDIENTS: LACTOSE, UNSPECIFIED FORM; SODIUM CHLORIDE

HIGHLIGHTS OF PRESCRIBING INFORMATION

These highlights do not include all the information needed to use HIBERIX safely and effectively. See full prescribing information for HIBERIX.
HIBERIX [Haemophilus b Conjugate Vaccine (Tetanus Toxoid Conjugate)] for injection, for intramuscular use
Initial U.S. Approval: 2009

RECENT MAJOR CHANGES

Dosage and Administration,; Reconstitution (2.2) Vial and Vial Presentation Removed | 12/2025

1 INDICATIONS AND USAGE

HIBERIX is a vaccine indicated for active immunization for the prevention of invasive disease caused by Haemophilus influenzae type b. HIBERIX is approved for use in children aged 6 weeks through 4 years (prior to fifth birthday). (1)

2 DOSAGE AND ADMINISTRATION

For intramuscular use.

A 4-dose series (approximately 0.5 mL each) given by intramuscular injection (2.1):

- Primary series: One dose each at 2, 4, and 6 months of age. The first dose may be given as early as 6 weeks of age.
- Booster: One dose at 15 through 18 months of age.

To prepare HIBERIX, reconstitute the Lyophilized Antigen Component only with the accompanying Sterile Saline Diluent. (2.2)

3 DOSAGE FORMS AND STRENGTHS

For injection. A single dose after reconstitution is approximately 0.5 mL. (3)

4 CONTRAINDICATIONS

Severe allergic reaction (e.g., anaphylaxis) after a previous dose of any H. influenzae type b- or tetanus toxoid-containing vaccine or any component of HIBERIX. (4)

5 WARNINGS AND PRECAUTIONS

- If Guillain-Barré syndrome has occurred within 6 weeks of receipt of a prior vaccine containing tetanus toxoid, the decision to give HIBERIX should be based on potential benefits and risks. (5.1)
- Syncope (fainting) can occur in association with administration of injectable vaccines, including HIBERIX. Procedures should be in place to avoid falling injury and to restore cerebral perfusion following syncope. (5.2)
- Apnea following intramuscular vaccination has been observed in some infants born prematurely. Decisions about when to administer an intramuscular vaccine, including HIBERIX, to infants born prematurely should be based on consideration of the individual infant’s medical status, and the potential benefits and possible risks of vaccination. (5.3)

6 ADVERSE REACTIONS

Common solicited adverse reactions (≥20%) were pain and redness at the injection site, irritability, drowsiness, fever, loss of appetite, fussiness, and restlessness. (6.1)

To report SUSPECTED ADVERSE REACTIONS, contact GlaxoSmithKline at 1-888-825-5249 or VAERS at 1-800-822-7967 or www.vaers.hhs.gov.

FULL PRESCRIBING INFORMATION

1 INDICATIONS AND USAGE

HIBERIX is indicated for active immunization for the prevention of invasive disease caused by Haemophilus influenzae (H. influenzae) type b. HIBERIX is approved for use in children aged 6 weeks through 4 years (prior to fifth birthday).

2 DOSAGE AND ADMINISTRATION

For intramuscular use.

2.1 Dose and Schedule

After reconstitution, a single dose of HIBERIX is approximately 0.5 mL [see Dosage and Administration (2.2)].

HIBERIX is administered as a 4-dose series. The series consists of a primary immunization course of 3 doses administered at 2, 4, and 6 months of age, followed by a booster dose administered at 15 through 18 months of age. The first dose may be given as early as 6 weeks of age.

2.2 Reconstitution

HIBERIX is supplied as a vial of Lyophilized Antigen Component and a prefilled syringe of Sterile Saline Diluent.

Reconstitute the Lyophilized Antigen Component only with the accompanying Sterile Saline Diluent to form HIBERIX.

Figure 1. Hold the ungraduated prefilled syringe of Sterile Saline Diluent by the barrel and unscrew the syringe cap by twisting it counterclockwise. Align the needle to the axis of the syringe and attach by gently connecting the needle hub into the Luer Lock Adaptor (LLA) and rotate a quarter turn clockwise until you feel it lock.

Figure 2. Cleanse the Lyophilized Antigen Component vial stopper. Transfer the entire contents of the prefilled syringe into the vial.

Figure 3. Shake the vial well until the powder is completely dissolved.

Figure 4. After reconstitution, withdraw the entire contents of reconstituted vaccine into the same syringe and after changing the needle administer the vaccine intramuscularly.

2.3 Administration

The reconstituted vaccine should be a clear and colorless solution. Parenteral drug products should be inspected visually for particulate matter and discoloration prior to administration, whenever solution and container permit. If either of these conditions exists, the vaccine should not be administered.

Administer HIBERIX intramuscularly immediately after reconstitution.

3 DOSAGE FORMS AND STRENGTHS

For injection.

A single dose after reconstitution is approximately 0.5 mL.

4 CONTRAINDICATIONS

Severe allergic reaction (e.g., anaphylaxis) after a previous dose of any H. influenzae type b- or tetanus toxoid-containing vaccine or any component of the vaccine is a contraindication to administration of HIBERIX [see Description (11)].

5 WARNINGS AND PRECAUTIONS

5.1 Guillain-Barré Syndrome

If Guillain-Barré syndrome has occurred within 6 weeks of receipt of a prior vaccine containing tetanus toxoid, the decision to give any tetanus toxoid-containing vaccine, including HIBERIX, should be based on careful consideration of the potential benefits and possible risks.

5.2 Syncope

Syncope (fainting) can occur in association with administration of injectable vaccines, including HIBERIX. Syncope can be accompanied by transient neurological signs such as visual disturbance, paresthesia, and tonic-clonic limb movements. Procedures should be in place to avoid falling injury and to restore cerebral perfusion following syncope.

5.3 Apnea in Premature Infants

Apnea following intramuscular vaccination has been observed in some infants born prematurely. Decisions about when to administer an intramuscular vaccine, including HIBERIX, to infants born prematurely should be based on consideration of the individual infant’s medical status, and the potential benefits and possible risks of vaccination.

5.4 Preventing and Managing Allergic Vaccine Reactions

Prior to administration, the healthcare provider should review the patient's immunization history for possible vaccine hypersensitivity. Epinephrine and other appropriate agents used for the control of immediate allergic reactions must be immediately available should an acute anaphylactic reaction occur.

5.5 Altered Immunocompetence

Safety and effectiveness of HIBERIX in immunosuppressed children have not been evaluated. If HIBERIX is administered to immunosuppressed children, including children receiving immunosuppressive therapy, the expected immune response may not be obtained.

5.6 Interference with Laboratory Tests

Urine antigen detection may not have a diagnostic value in suspected disease due to H. influenzae type b within 1 to 2 weeks after receipt of a H. influenzae type b-containing vaccine, including HIBERIX [see Drug Interactions (7.1)].

5.7 Tetanus Immunization

Immunization with HIBERIX does not substitute for routine tetanus immunization.

6 ADVERSE REACTIONS

6.1 Clinical Trials Experience

Because clinical trials are conducted under widely varying conditions, adverse reaction rates observed in the clinical trials of a vaccine cannot be directly compared with rates in the clinical trials of another vaccine and may not reflect the rates observed in practice. There is the possibility that broad use of HIBERIX could reveal adverse reactions not observed in clinical trials.

Across clinical trials, common solicited adverse reactions (≥20%) were pain and redness at the injection site, irritability, drowsiness, fever, loss of appetite, fussiness, and restlessness.

Study 1: In a randomized, controlled clinical trial conducted in the U.S., children were vaccinated with HIBERIX (n = 2,963), a U.S.-licensed monovalent Haemophilus b Conjugate Vaccine (Control PRP-T) (Sanofi Pasteur SA) (n = 520), or a U.S.-licensed combined Diphtheria and Tetanus Toxoids and Acellular Pertussis Adsorbed, Inactivated Poliovirus and Haemophilus b Conjugate Vaccine (DTaP-IPV/Hib) (Sanofi Pasteur Ltd.) (n = 520) at 2, 4, and 6 months of age. HIBERIX and Control PRP-T (Sanofi Pasteur SA) were administered concomitantly with PEDIARIX (DTaP-HBV-IPV) [Diphtheria and Tetanus Toxoids and Acellular Pertussis Adsorbed, Hepatitis B (Recombinant) and Inactivated Poliovirus Vaccine] and Pneumococcal 13-valent Conjugate Vaccine (PCV13) (Wyeth Pharmaceuticals Inc.) with Doses 1, 2, and 3 and ROTARIX [Rotavirus Vaccine, Live, Oral] with Doses 1 and 2. DTaP-IPV/Hib was administered concomitantly with PCV13 and ENGERIX‑B [Hepatitis B Vaccine (Recombinant)] with Doses 1, 2, and 3 and ROTARIX with Doses 1 and 2. If a birth dose of hepatitis B vaccine was received, ENGERIX-B was given with Doses 1 and 3. In the total population, 51.2% were male; 61% were white, 8% were Asian, 9% were black, and 22% were other racial/ethnic groups.

In Study 1, children received a booster dose of either HIBERIX (n = 2,336), a Haemophilus b Conjugate Vaccine (Control PRP-T) (Sanofi Pasteur SA) (n = 435), or a combined Diphtheria and Tetanus Toxoids and Acellular Pertussis Adsorbed, Inactivated Poliovirus and Haemophilus b Conjugate Vaccine (DTaP-IPV/Hib) (Sanofi Pasteur Ltd.) (n = 400) at 15 to 18 months of age (mean age: 15.6 months) following primary vaccination at 2, 4, and 6 months of age with the same vaccine. The booster dose of HIBERIX and Control PRP-T (Sanofi Pasteur SA) was administered concomitantly with INFANRIX (DTaP) [Diphtheria and Tetanus Toxoids and Acellular Pertussis Vaccine Adsorbed].

In 7 additional clinical studies, 1,008 children received HIBERIX as a booster dose following primary vaccination with either HIBERIX (n = 530), Haemophilus b Conjugate Vaccine (Control PRP-T) (Sanofi Pasteur SA) (n = 235), Haemophilus b Conjugate Vaccine (Merck & Co., Inc.) (n = 26), or Haemophilus b Conjugate Vaccine (Wyeth Pharmaceuticals Inc.) (no longer licensed in the U.S., n = 217). None of the studies included a comparator group that received a booster dose with a U.S.-licensed Haemophilus b Conjugate Vaccine. Studies were conducted in Europe, Canada, and Latin America. Across these studies, the mean age of subjects at the time of booster vaccination with HIBERIX ranged from 16 to 19 months. At the time of vaccination, 172 (17.1%) subjects were aged 11 to 14 months, 642 (63.7%) subjects were aged 15 to 18 months, and 194 (19.2%) subjects were aged 19 to 25 months. Approximately half of the subjects were male. Among subjects for whom information on race/ethnicity was available, nearly all subjects were white.

In these 7 studies, HIBERIX was administered concomitantly with non-U.S. formulations (containing 2.5 mg 2-phenoxyethanol per dose as preservative) of one of the following U.S.-licensed vaccines: INFANRIX (DTaP) [Diphtheria and Tetanus Toxoids and Acellular Pertussis Vaccine Adsorbed], KINRIX (DTaP-IPV) [Diphtheria and Tetanus Toxoids and Acellular Pertussis Adsorbed and Inactivated Poliovirus Vaccine], or PEDIARIX (DTaP-HBV-IPV). In the studies, DTaP-IPV and DTaP-HBV-IPV were administered in dosing regimens not approved in the U.S. Some subjects received DTaP-HBV (GlaxoSmithKline Biologicals, not licensed in U.S.) concomitantly with HIBERIX.

Solicited Adverse Reactions

The reported frequencies of solicited local reactions and general adverse reactions from Study 1 after primary and booster vaccination are presented in Table 1 and Table 2, respectively.

Table 1. Percentage of Children with Solicited Local Reactions and General Adverse Reactions within 4 Days of Primary Series Vaccinationa (at 2, 4, and 6 Months of Age) with HIBERIXb, Control PRP-Tb, or DTaP-IPV/Hibc, Total Vaccinated Cohortd
Adverse Reactions | HIBERIX; % |  |  | Control PRP-T; % |  |  | DTaP-IPV/Hib; %
Adverse Reactions | Dose |  |  | Dose |  |  | Dose
Adverse Reactions | 1 | 2 | 3 | 1 | 2 | 3 | 1 | 2 | 3
Locale
n | 2,828 | 2,668 | 2,553 | 498 | 481 | 463 | 492 | 469 | 443
Pain | 49 | 45 | 43 | 57 | 53 | 48 | 58 | 50 | 49
Pain, Grade 3f | 4 | 3 | 2 | 9 | 5 | 4 | 9 | 3 | 3
Redness | 19 | 25 | 29 | 24 | 32 | 30 | 26 | 31 | 37
Redness, >20 mm | 1 | 1 | 1 | 2 | 1 | 0 | 2 | 2 | 2
Swelling | 13 | 15 | 19 | 19 | 22 | 20 | 20 | 24 | 24
Swelling, >20 mm | 2 | 1 | 1 | 4 | 3 | 1 | 4 | 2 | 2
General
n | 2,830 | 2,669 | 2,553 | 499 | 480 | 463 | 492 | 469 | 443
Irritability | 69 | 70 | 67 | 76 | 71 | 67 | 73 | 67 | 69
Irritability, Grade 3g | 4 | 6 | 5 | 8 | 8 | 5 | 6 | 5 | 3
Drowsiness | 60 | 54 | 49 | 66 | 56 | 50 | 61 | 52 | 50
Drowsiness, Grade 3h | 2 | 3 | 2 | 4 | 2 | 1 | 4 | 3 | 3
Loss of appetite | 29 | 28 | 28 | 33 | 32 | 27 | 34 | 24 | 24
Loss of appetite, Grade 3i | 1 | 2 | 2 | 2 | 1 | 0 | 1 | 0 | 1
Fever | 14 | 19 | 19 | 16 | 19 | 16 | 12 | 11 | 18
Fever, Grade 3j | 0 | 1 | 1 | 0 | 0 | 1 | 0 | 0 | 1
n = All subjects for whom safety data were available.
a Within 4 days of vaccination defined as day of vaccination and the next 3 days.
b Each dose (Doses 1, 2, and 3) of HIBERIX or Control PRP-T (Sanofi Pasteur SA) was concomitantly administered with PEDIARIX (DTaP-HBV-IPV) and PCV13. Doses 1 and 2 were concomitantly administered with ROTARIX.
c Each dose (Doses 1, 2, and 3) of DTaP-IPV/Hib was concomitantly administered with PCV13 and ENGERIX-B with Doses 1, 2, and 3 and ROTARIX with Doses 1 and 2. If a birth dose of hepatitis B vaccine was received, ENGERIX-B was given with Doses 1 and 3.
d Study 1: NCT01000974.
e Local reactions at the injection site for HIBERIX, Control PRP-T, or DTaP-IPV/Hib.
f Grade 3 pain defined as cried when limb was moved/spontaneously painful.
g Grade 3 irritability defined as crying that could not be comforted/prevented normal activity.
h Grade 3 drowsiness defined as prevented normal daily activity.
i Grade 3 loss of appetite defined as did not eat at all.
j Fever defined as ≥100.4°F (≥38.0°C) rectally; Grade 3 fever defined as >103.1°F (>39.5°C) rectally.

Table 2. Percentage of Children with Solicited Local Reactions and General Adverse Reactions within 4 Days of Booster Vaccinationa (Dose 4 at 15 through 18 Months of Age) with HIBERIXb, Control PRP-Tb, or DTaP-IPV/Hib, Total Vaccinated Cohortc
Adverse Reactions | HIBERIX; % |  | Control PRP-T; % |  | DTaP-IPV/Hib%
Adverse Reactions | Any | Grade 3d | Any | Grade 3d | Any | Grade 3d
Locale | n = 2,224 |  | n = 416 |  | n = 379
Pain | 41 | 1 | 43 | 1 | 43 | 2
Redness | 30 | 0 | 31 | 1 | 30 | 3
Swelling | 18 | 1 | 20 | 1 | 20 | 3
General | n = 2,225 |  | n = 416 |  | n = 379
Irritability | 58 | 2 | 60 | 5 | 53 | 2
Drowsiness | 39 | 1 | 39 | 3 | 31 | 0
Loss of appetite | 28 | 1 | 34 | 2 | 22 | 1
Feverf | 15 | 1 | 14 | 1 | 18 | 1
n = All subjects for whom safety data were available.
Subjects received primary vaccination at 2, 4, and 6 months of age with the same vaccine as the booster dose.
a Within 4 days of vaccination defined as day of vaccination and the next 3 days.
b The booster dose of HIBERIX and Control PRP-T (Sanofi Pasteur SA) was concomitantly administered with INFANRIX (DTaP).
c Study 1: NCT01000974.
d Grade 3 pain defined as cried when limb was moved/spontaneously painful.
Grade 3 redness, swelling defined as >20 mm.
Grade 3 irritability defined as crying that could not be comforted/prevented normal activity.
Grade 3 drowsiness defined as prevented normal daily activity.
Grade 3 loss of appetite defined as did not eat at all.
Grade 3 fever defined as >102.2°F (>39.0°C) axillary.
e Local reactions at the injection site for HIBERIX, Control PRP-T, or DTaP-IPV/Hib.
f Fever defined as ≥99.5°F (≥37.5°C) axillary.

In an open-label, multicenter study conducted in Germany (Study 2), 371 children received a booster dose of HIBERIX administered concomitantly with DTaP-HBV-IPV. The mean age at the time of vaccination was 16 months. Subjects in this study had previously received a primary series with either HIBERIX (n = 92), Control PRP-T (Sanofi Pasteur SA) (n = 96), or Haemophilus b Conjugate Vaccine (Wyeth Pharmaceuticals Inc.) (no longer licensed in the U.S.) (n = 183). All subjects previously received 3 doses of DTaP-HBV-IPV. The reported frequencies of solicited local reactions and general adverse reactions are presented in Table 3.

Table 3. Percentage of Children with Solicited Local Reactions and General Adverse Reactions within 4 Days of Booster Vaccinationa (Dose 4) with HIBERIXb Coadministered with DTaP-HBV-IPVc, Intent-to-Treat Cohort (n = 371)
 | % | %
Adverse Reactions | Any | Grade 3
Locald
Redness | 25 | 2e
Pain | 21 | 1f
Swelling | 15 | 2e
General
Feverg | 35 | 4
Fussiness | 26 | 1h
Loss of appetite | 23 | 1i
Restlessness | 22 | 1i
Sleepiness | 20 | 1i
Diarrhea | 15 | 1i
Vomiting | 5 | 1i
n = All subjects for whom safety data were available.
a Within 4 days of vaccination defined as day of vaccination and the next 3 days.
b In this study, 92 subjects previously received 3 doses of HIBERIX, 96 subjects previously received 3 doses of a Control PRP-T (Sanofi Pasteur SA), and 183 subjects previously received 3 doses of a Haemophilus b Conjugate Vaccine that is no longer licensed in the U.S.
c In this study, DTaP-HBV-IPV was given to subjects who previously received 3 doses of DTaP-HBV-IPV. In the U.S., PEDIARIX is approved for use as a 3-dose primary series; use as a fourth consecutive dose is not approved in the U.S.
d Local reactions at the injection site for HIBERIX.
e Grade 3 redness or swelling defined as >20 mm.
f Grade 3 pain defined as causing crying when limb moved.
g Fever defined as ≥100.4°F (≥38.0°C) rectally or ≥99.5°F (≥37.5°C) axillary, oral, or tympanic; Grade 3 fever defined as >103.1°F (>39.5°C) rectally or >102.2°F (>39.0°C) axillary, oral, or tympanic.
h Grade 3 fussiness defined as persistent crying and could not be comforted.
i Grade 3 for these symptoms defined as preventing normal daily activity.

Serious Adverse Reactions

In Study 1, one of 2,963 subjects who received HIBERIX and coadministered vaccines given at 2, 4, and 6 months of age experienced a serious adverse reaction which was in temporal association with vaccination and had no alternative plausible causes (convulsion on Day 14 after Dose 1). One of 2,336 subjects who received a booster dose of HIBERIX concomitantly with INFANRIX experienced a serious adverse reaction which was in temporal association with vaccination and had no alternative plausible causes (new onset febrile seizure on Day 1 after Dose 4).

In the 7 additional studies, 2 of 1,008 subjects reported a serious adverse reaction that occurred in the 31-day period following booster immunization with HIBERIX. One subject developed bilateral pneumonia 9 days post-vaccination and one subject experienced asthenia following accidental drug ingestion 18 days post-vaccination.

6.2 Postmarketing Experience

In addition to reports in clinical trials for HIBERIX, the following adverse reactions have been identified during postapproval use of HIBERIX. Because these reactions are reported voluntarily from a population of uncertain size, it is not possible to reliably estimate their frequency or establish a causal relationship to vaccination.

General Disorders and Administration Site Conditions

Extensive swelling of the vaccinated limb, injection site induration.

Immune System Disorders

Allergic reactions (including anaphylactic and anaphylactoid reactions), angioedema.

Nervous System Disorders

Convulsions (with or without fever), hypotonic-hyporesponsive episode (i.e., sudden onset of hypotonia, hyporesponsiveness, and pallor or cyanosis), somnolence, syncope, or vasovagal responses to injection.

Respiratory, Thoracic, and Mediastinal Disorders

Apnea [see Warnings and Precautions (5.3)].

Skin and Subcutaneous Tissue Disorders

Rash, urticaria.

7 DRUG INTERACTIONS

7.1 Interference with Laboratory Tests

Haemophilus b capsular polysaccharide derived from Haemophilus b Conjugate Vaccines has been detected in the urine of some vaccinees.^1 Urine antigen detection may not have a diagnostic value in suspected disease due to H. influenzae type b within 1 to 2 weeks after receipt of a H. influenzae type b-containing vaccine, including HIBERIX [see Warnings and Precautions (5.6)].

7.2 Concomitant Vaccine Administration

In clinical studies, HIBERIX was administered concomitantly with routinely recommended pediatric vaccines [see Clinical Studies (14.2)].

7.3 Immunosuppressive Therapies

Immunosuppressive therapies, including irradiation, antimetabolites, alkylating agents, cytotoxic drugs, and corticosteroids (used in greater than physiologic doses), may reduce the immune response to HIBERIX.

8 USE IN SPECIFIC POPULATIONS

8.4 Pediatric Use

Safety and effectiveness of HIBERIX in children younger than 6 weeks and in children aged 5 to 16 years have not been established.

11 DESCRIPTION

HIBERIX [Haemophilus b Conjugate Vaccine (Tetanus Toxoid Conjugate)] is a solution for intramuscular injection, supplied as a sterile, lyophilized powder which is reconstituted at the time of use with the accompanying saline diluent. HIBERIX contains Haemophilus b capsular polysaccharide (polyribosyl‑ribitol‑phosphate [PRP]), a high molecular weight polymer prepared from the H. influenzae type b strain 20,752 grown in a synthetic medium that undergoes heat inactivation and purification. The tetanus toxin, prepared from Clostridium tetani grown in a semi‑synthetic medium, is detoxified with formaldehyde and purified. The capsular polysaccharide is covalently bound to the tetanus toxoid. After purification, the conjugate is lyophilized in the presence of lactose as a stabilizer. The diluent for HIBERIX is a sterile saline solution (0.9% sodium chloride) supplied in prefilled syringes.

After reconstitution, each approximately 0.5‑mL dose of HIBERIX contains 10 mcg of purified capsular polysaccharide conjugated to approximately 25 mcg of tetanus toxoid, 12.6 mg of lactose, and ≤0.5 mcg of residual formaldehyde.

HIBERIX does not contain a preservative.

The stopper of the vial containing Lyophilized Antigen Component and the tip cap and rubber plunger stopper of the prefilled syringe containing Sterile Saline Diluent are not made with natural rubber latex.

12 CLINICAL PHARMACOLOGY

12.1 Mechanism of Action

H. influenzae is a gram-negative coccobacillus. Most strains of H. influenzae that cause invasive disease are type b. H. influenzae type b can cause invasive disease such as sepsis and meningitis.

Specific levels of antibodies to polyribosyl-ribitol-phosphate (anti-PRP) have been shown to correlate with protection against invasive disease due to H. influenzae type b. Based on data from passive antibody studies^2 and a clinical efficacy study with unconjugated Haemophilus b polysaccharide vaccine^3, an anti-PRP concentration of 0.15 mcg/mL has been accepted as a minimal protective level. Data from an efficacy study with unconjugated Haemophilus b polysaccharide vaccine indicate that an anti-PRP concentration of ≥1.0 mcg/mL predicts protection through at least a 1-year period.^4,5 These antibody levels have been used to evaluate the effectiveness of Haemophilus b Conjugate Vaccines, including HIBERIX.

13 NONCLINICAL TOXICOLOGY

13.1 Carcinogenesis, Mutagenesis, Impairment of Fertility

HIBERIX has not been evaluated for carcinogenic or mutagenic potential, or for impairment of fertility.

14 CLINICAL STUDIES

14.1 Immunological Evaluation

Primary Series Vaccination (Doses 1, 2, and 3)

The immunogenicity of HIBERIX was evaluated in a randomized, controlled trial (Study 1). HIBERIX or control vaccines were administered concomitantly with U.S.-licensed vaccines [see Adverse Reactions (6.1)].

Anti-PRP geometric mean concentrations (GMCs) and seroprotection rates 1 month following Dose 3 of HIBERIX, Control PRP-T (Sanofi Pasteur SA), or DTaP-IPV/Hib are presented in Table 4.

Table 4. Anti-PRP GMCs and Seroprotection Rates 1 Month following 3 Doses of HIBERIX, Control PRP-Ta, or DTaP-IPV/Hibb Administered at 2, 4, and 6 Months of Age, ATP Cohort for Immunogenicityc
Vaccine | n | Anti-PRP GMC; (mcg/mL); (95% CI) | % Anti-PRP; ≥0.15 mcg/mL; (95% CI) | % Anti-PRP; ≥1.0 mcg/mL; (95% CI)
HIBERIX | 1,590 | 5.19; (4.77, 5.66) | 96.6; (95.6, 97.4) | 81.2; (79.2, 83.1)
Control PRP-T | 274 | 6.74; (5.59, 8.13) | 96.7d; (93.9, 98.5) | 89.8e; (85.6, 93.1)
DTaP-IPV/Hib | 253 | 3.64; (2.89, 4.58) | 92.5f; (88.5, 95.4) | 78.3f; (72.7, 83.2)
a U.S.-licensed monovalent Haemophilus b Conjugate Vaccine (Control PRP-T) (Sanofi Pasteur SA).
b U.S.-licensed DTaP-IPV/Hib Vaccine (Sanofi Pasteur Ltd.).
c Study 1: NCT01000974.
d HIBERIX was non-inferior to Control PRP-T for percent of subjects achieving anti-PRP ≥0.15 mcg/mL (lower limit of 95% CI on difference of HIBERIX minus Control PRP-T ≥ predefined limit of -5%).
e The non-inferiority criterion was not met (lower limit of 95% CI for the difference in the percentages of subjects with anti-PRP ≥1.0 mcg/mL between two groups [HIBERIX minus Control PRP-T] was -12.28%, which was lower than the predefined limit of -10%).
f Analyses of anti-PRP immune responses following DTaP-IPV/Hib vaccination were exploratory.

Booster Vaccination (Dose 4)

The immunogenicity of HIBERIX administered as a booster dose at 15 to 18 months of age was evaluated in a subset of children from Study 1 (n = 336) in comparison with U.S.-licensed vaccines following primary vaccination at 2, 4, and 6 months of age [see Adverse Reactions (6.1)]. The booster dose of HIBERIX and Control PRP-T (Sanofi Pasteur SA) was administered concomitantly with INFANRIX.

Antibodies to PRP were measured in sera obtained immediately prior to and 1 month after booster vaccination with HIBERIX or the control vaccines. Anti-PRP GMCs and seroprotection rates are presented in Table 5.

Table 5. Anti-PRP GMCs and Seroprotection Rates prior to and 1 Month following a Booster Dose (Dose 4 at 15 through 18 Months of Age) of HIBERIX, Control PRP-Ta, or DTaP-IPV/Hibb, ATP Cohort for Immunogenicityc
Vaccine | n | Anti-PRP GMC |  | % Anti-PRP |  | % Anti-PRP
Vaccine | n | (mcg/mL); (95% CI) |  | ≥0.15 mcg/mL; (95% CI) |  | ≥1.0 mcg/mL; (95% CI)
Vaccine | n | Pre- | Post- | Pre- | Post- | Pre- | Post-
HIBERIX | 329-336 | 0.50; (0.42, 0.59) | 48.78; (42.0, 56.66) | 75.1; (70.0, 79.7) | 100.0; (98.9, 100.0) | 32.2; (27.2, 37.6) | 99.1; (97.4, 99.8)
Control PRP-T | 226-236 | 0.47; (0.38, 0.57) | 40.29; (33.39, 48.63) | 76.1; (70.0, 81.5) | 99.6; (97.7, 100.0) | 27.0; (21.3, 33.3) | 97.9d; (95.1, 99.3)
DTaP-IPV/Hib | 175-186 | 0.38; (0.30, 0.48) | 37.54; (30.53, 46.16) | 66.3; (58.8, 73.2) | 100.0; (98.0, 100.0) | 25.1; (18.9, 32.2) | 98.9e; (96.2, 99.9)
a U.S.-licensed monovalent Haemophilus b Conjugate Vaccine (Control PRP-T) (Sanofi Pasteur SA).
b U.S.-licensed DTaP-IPV/Hib Vaccine (Sanofi Pasteur Ltd.).
c Study 1: NCT01000974.
d HIBERIX was non-inferior to Control PRP-T for percent of subjects achieving anti-PRP ≥1.0 mcg/mL (lower limit of 97.5% CI on difference of HIBERIX minus Control PRP-T ≥predefined limit of -10%) at 1 month following the booster dose.
e Analyses of anti-PRP immune responses following DTaP-IPV/Hib vaccination were exploratory.

In 6 additional clinical studies, the immune response to HIBERIX administered as a booster dose was evaluated in a total of 415 children aged 12 to 23 months. At the time of vaccination, 30 children were aged 12 to 14 months, 316 children were aged 15 to 18 months, and 69 children were aged 19 to 23 months. Among subjects, 43% to 60% were male. Among subjects for whom information on race/ethnicity was available, nearly all subjects were white. None of the studies included a comparator group that received a booster dose with a U.S.-licensed Haemophilus b Conjugate Vaccine. Characteristics of 3 of these studies are presented in Table 6.

Table 6. Characteristics of 3 Open-Label Booster Immunization Studies of HIBERIX
Study | Country | Per‑Protocol Immunogenicity Cohort n | Priming History | Booster Vaccination with HIBERIX
Study | Country | Per‑Protocol Immunogenicity Cohort n | Priming History | Age at Vaccination (months) | Concomitantly Administered Vaccinea
3 | Canada | 42 | DTaP-HBV-IPVb + Haemophilus b Conjugate Vaccinec; at 2, 4, and 6 months of age | 16-18 | DTaP-HBV-IPVb
4 | Canada | 64 | DTaP-IPVd + HIBERIX; at 2, 4, and 6 months of age | 16-19 | DTaP-IPVd
5 | Germany | 108 | DTaP-HBVe + HIBERIX; at 3, 4, and 5 months of age | 16-23 | DTaP-HBVe
a Administered at a separate site.
b Non-U.S. formulation equivalent to PEDIARIX with the exception of containing 2.5 mg 2-phenoxyethanol per dose as preservative. In the U.S., PEDIARIX is approved for use as a 3-dose primary series; use as a fourth consecutive dose is not approved in the U.S.
c U.S.-licensed Haemophilus b Conjugate Vaccine (Control PRP-T) (Sanofi Pasteur SA).
d Non-U.S. formulation equivalent to KINRIX with the exception of containing 2.5 mg 2-phenoxyethanol per dose as preservative. In the U.S., KINRIX is approved for use as the fifth dose of DTaP and the fourth dose of IPV in children aged 4 to 6 years previously primed with approved dosing regimens of INFANRIX and/or PEDIARIX. The DTaP-IPV dosing regimen is not approved in the U.S.
e Manufactured by GlaxoSmithKline Biologicals (not licensed in the U.S.).

Antibodies to PRP were measured in sera obtained immediately prior to and 1 month after booster vaccination with HIBERIX. Geometric mean concentrations and anti-PRP seroprotection rates are presented in Table 7.

Table 7. Anti-PRP GMCs and Seroprotection Rates prior to and 1 Month following a Booster Dose of HIBERIX, Per-Protocol Immunogenicity Cohort
 |  | Anti-PRP GMC |  | % Anti-PRP |  | % Anti-PRP
 |  | (mcg/mL) |  | ≥0.15 mcg/mL |  | ≥1.0 mcg/mL
Study | n | Pre- | Post- | Pre- | Post- | Pre- | Post-
3a | 42 | 0.46 | 59.07 | 76.2 | 100 | 35.7 | 97.6
4b | 63-64 | 0.25 | 47.78 | 71.4 | 100 | 12.7 | 100
5c | 108 | 0.59 | 96.12 | 77.8 | 100 | 32.4 | 100
GMC = Geometric mean antibody concentration.
n = Number of children for whom serological results were available for the pre- and post-dose immunological evaluations.
Studies 3, 4, and 5 correspond to Studies 3, 4, and 5, respectively in Table 6.
a Canadian study in children aged 16 to 18 months who previously received 3 doses of DTaP-HBV-IPV and Haemophilus b Conjugate Vaccine (Control PRP-T) (Sanofi Pasteur SA). The booster dose of HIBERIX was coadministered with DTaP-HBV-IPV (a fourth consecutive dose of PEDIARIX is not approved in the U.S.). In this study, pre-vaccination sera may have been obtained up to 1 week prior to booster vaccination with HIBERIX.
b Canadian study in children aged 16 to 19 months who previously received 3 doses of DTaP-IPV and HIBERIX. The booster dose of HIBERIX was coadministered with DTaP-IPV. The DTaP-IPV dosing regimen is not approved in the U.S.
c German study in children aged 16 to 23 months who previously received 3 doses of DTaP-HBV (GlaxoSmithKline Biologicals, not licensed in the U.S.) and HIBERIX. The booster dose of HIBERIX was coadministered with DTaP-HBV.

14.2 Concomitant Vaccine Administration

Primary Series Vaccination (Doses 1, 2, and 3)

In U.S. Study 1, subjects who received HIBERIX concomitantly with PEDIARIX (DTaP-HBV-IPV) and PCV13 at 2, 4, and 6 months of age had no evidence for reduced antibody responses relative to the response in control subjects administered Control PRP-T (Sanofi Pasteur SA) concomitantly with PEDIARIX (DTaP-HBV-IPV) and PCV13, to pertussis antigens (GMC to pertussis toxin, filamentous hemagglutinin, and pertactin), diphtheria toxoid (antibody levels ≥0.1 IU/mL), tetanus toxoid (antibody levels ≥0.1 IU/mL), poliovirus types 1, 2, and 3 (antibody levels ≥1:8 to each virus), PCV13 (antibody levels ≥0.2 mcg/mL and GMC to each serotype), or hepatitis B (anti-hepatitis B surface antigen ≥10 mIU/mL). The immune responses to PEDIARIX (DTaP-HBV-IPV) and PCV13 were evaluated 1 month following Dose 3. Subjects in both groups received ROTARIX at 2 and 4 months of age.

Booster Vaccination (Dose 4)

In U.S. Study 1, subjects who received a booster dose of HIBERIX concomitantly with INFANRIX at 15 to 18 months of age had no evidence for reduced antibody responses to pertussis antigens (GMC to pertussis toxin, filamentous hemagglutinin, and pertactin), diphtheria toxoid (antibody levels ≥0.1 IU/mL), and tetanus toxoid (antibody levels ≥0.1 IU/mL), relative to the responses in control subjects administered Control PRP-T (Sanofi Pasteur SA) concomitantly with INFANRIX.

In 7 additional studies, a booster dose of HIBERIX was administered concomitantly with non-U.S. formulations of INFANRIX, KINRIX, and PEDIARIX. Non-U.S. formulations of KINRIX and PEDIARIX were administered in dosing regimens not approved in the U.S.

Sufficient data are not available to confirm lack of interference in immune responses to vaccines other than INFANRIX administered concomitantly with a booster dose of HIBERIX.

15 REFERENCES

1. Rothstein EP, Madore DV, Girone JAC, et al. Comparison of antigenuria after immunization with three Haemophilus influenzae type b conjugate vaccines. Pediatr Infect Dis J. 1991;10:311-314.
2. Robbins JB, Parke JC, Schneerson R, et al. Quantitative measurement of “natural” and immunization-induced Haemophilus influenzae type b capsular polysaccharide antibodies. Pediatr Res. 1973;7:103-110.
3. Peltola H, Käythy H, Sivonen A, et al. Haemophilus influenzae type b capsular polysaccharide vaccine in children: A double-blind field study of 100,000 vaccinees 3 months to 5 years of age in Finland. Pediatrics. 1977;60:730-737.
4. Käythy H, Peltola H, Karanko V, et al. The protective level of serum antibodies to the capsular polysaccharide of Haemophilus influenzae type b. J Infect Dis. 1983;147:1100.
5. Anderson P. The protective level of serum antibodies to the capsular polysaccharide of Haemophilus influenzae type b. J Infect Dis. 1984;149:1034.

16 HOW SUPPLIED/STORAGE AND HANDLING

HIBERIX is supplied in a carton (NDC 58160‑726‑15) containing:

- 10 single‑dose vials of Lyophilized Antigen Component: NDC 58160‑816‑03.
- 10 single‑dose, prefilled, ungraduated TIP‑LOK syringes (Luer Lock syringes) of Sterile Saline Diluent packaged without needles NDC 58160‑817‑02.

TIP‑LOK syringes are to be used with Luer Lock compatible needles.

The stopper of the vial containing Lyophilized Antigen Component and the tip cap and rubber plunger stopper of the prefilled syringe containing Sterile Saline Diluent are not made with natural rubber latex.

16.1 Storage before Reconstitution

Lyophilized Antigen Component vials: Store refrigerated between 2° and 8°C (36° and 46°F). Protect vials from light.

Sterile Saline Diluent prefilled syringes: Store refrigerated or at controlled room temperature between 2° and 25°C (36° and 77°F). Do not freeze. Discard if the diluent has been frozen.

17 PATIENT COUNSELING INFORMATION

- Inform parents or guardians of the potential benefits and risks of immunization with HIBERIX.
- Inform parents or guardians about the potential for adverse reactions that have been temporally associated with administration of HIBERIX or other vaccines containing similar components.
- Give parents or guardians the Vaccine Information Statements, which are required by the National Childhood Vaccine Injury Act of 1986 to be given prior to immunization. These materials are available free of charge at the Centers for Disease Control and Prevention (CDC) website (www.cdc.gov/vaccines).

Trademarks are owned by or licensed to the GSK group of companies.

Manufactured by GlaxoSmithKline Biologicals

Rixensart, Belgium, U.S. License 1617, and

Distributed by GlaxoSmithKline

Durham, NC 27701

©2025 GSK group of companies or its licensor.

HRX:11PI

PACKAGE LABEL

PRINCIPAL DISPLAY PANEL

NDC 58160-818-11

HIBERIX

Haemophilus b Conjugate Vaccine (Tetanus Toxoid Conjugate)

Hib

Rx only

For Use from 6 weeks through 4 years of age

Contents (see back panel for storage instructions):

10 Vials of Lyophilized Vaccine

10 Vials of Sterile Saline Diluent (for reconstitution of Lyophilized Vaccine).

Lyophilized Vaccine Made in Singapore

©2020 GSK group of companies or its licensor.

Rev. 11/20

504484

PACKAGE LABEL

PRINCIPAL DISPLAY PANEL

NDC 58160-726-15

HIBERIX

Haemophilus b Conjugate Vaccine (Tetanus Toxoid Conjugate)

Hib

Rx only

GSK

For Use from 6 weeks through 4 years of age

Contents 10 Doses of HIBERIX:

- 10 Single-dose vials each containing one dose of Lyophilized Antigen Component
- 10 Single-dose prefilled ungraduated TIP-LOK syringes of Sterile Saline Diluent (0.9% NaCl)

After reconstitution, a single dose of HIBERIX is approximately 0.5 mL

TIP-LOK syringes to be used with Luer Lock compatible needles

NEEDLES NOT INCLUDED

©2023 GSK group of companies or its licensor.

Made in Singapore

Rev. 11/23

517080